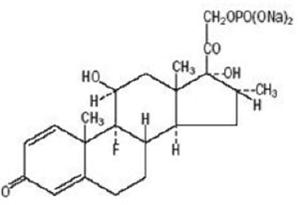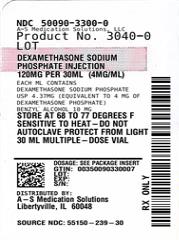 DRUG LABEL: DEXAMETHASONE SODIUM PHOSPHATE
NDC: 50090-3300 | Form: INJECTION, SOLUTION
Manufacturer: A-S Medication Solutions
Category: prescription | Type: Human Prescription Drug Label
Date: 20260224

ACTIVE INGREDIENTS: DEXAMETHASONE SODIUM PHOSPHATE 4 mg/1 mL
INACTIVE INGREDIENTS: BENZYL ALCOHOL; SODIUM SULFITE; ANHYDROUS TRISODIUM CITRATE; ANHYDROUS CITRIC ACID; SODIUM HYDROXIDE; WATER

Dexamethasone Sodium Phosphate Injection USP

Rx only

DESCRIPTION

Dexamethasone sodium phosphate injection USP is a sterile, clear, colorless solution, free from visible particles and a water-soluble inorganic ester of dexamethasone which produces a rapid response even when injected intramuscularly.
Dexamethasone Sodium Phosphate USP, C22H28FNa2O8P, has a molecular weight of 516.41 and chemically is Pregn-4-ene-3, 20-dione, 9-fluoro-11, 17-dihydroxy-16-methyl-21 (phosphonooxy)-, disodium salt, (11β, 16α).
It occurs as a white to practically white powder, is exceedingly hygroscopic, is soluble in water and its solutions have a pH between 7.0 and 8.5. It has the following structural formula:
Dexamethasone sodium phosphate injection USP is available in 4 mg/mL concentration.
Each mL of dexamethasone sodium phosphate injection USP, 4 mg/mL, contains 4.37 mg of dexamethasone sodium phosphate, USP equivalent to 4 mg dexamethasone phosphate; 1 mg sodium sulfite; 10 mg benzyl alcohol (preservative). Made isotonic with sodium citrate. pH adjusted with citric acid or sodium hydroxide.
ACTIONS — Naturally occurring glucocorticoids (hydrocortisone), which also have salt-retaining properties, are used as replacement therapy in adrenocortical deficiency states. Their synthetic analogs are primarily used for their potent anti-inflammatory effects in disorders of many organ systems.
Glucocorticoids cause profound and varied metabolic effects. In addition, they modify the body’s immune responses to diverse stimuli.

INDICATIONS AND USAGE

A. Intravenous or intramuscular administration. When oral therapy is not feasible and the strength, dosage form, and route of administration of the drug reasonably lend the preparation to the treatment of the condition, those products labeled for intravenous or intramuscular use are indicated as follows:

1. Endocrine disorders. Primary or secondary adrenocortical insufficiency (hydrocortisone or cortisone is the drug of choice; synthetic analogs may be used in conjunction with mineralocorticoids where applicable; in infancy, mineralocorticoid supplementation is of particular importance).

Acute adrenocortical insufficiency (hydrocortisone or cortisone is the drug of choice; mineralocorticoid supplementation may be necessary, particularly when synthetic analogs are used).

Preoperatively, and in the event of serious trauma or illness, in patients with known adrenal insufficiency or when adrenocortical reserve is doubtful.

Shock unresponsive to conventional therapy if adrenocortical insufficiency exists or is suspected.

Congenital adrenal hyperplasia.

Nonsuppurative thyroiditis.

Hypercalcemia associated with cancer.

2. Rheumatic disorders. As adjunctive therapy for short-term administration (to tide the patient over an acute episode or exacerbation) in:

Post-traumatic osteoarthritis.

Synovitis of osteoarthritis.

Rheumatoid arthritis, including juvenile rheumatoid arthritis (selected cases may require low-dose maintenance therapy).

Acute and subacute bursitis.

Epicondylitis.

Acute nonspecific tenosynovitis.

Acute gouty arthritis.

Psoriatic arthritis.

Ankylosing spondylitis.

3. Collagen diseases. During an exacerbation or as maintenance therapy in selected cases of:

Systemic lupus erythematosus.
Acute rheumatic carditis.

4. Dermatologic diseases.

Pemphigus.

Severe erythema multiforme (Stevens-Johnson Syndrome).

Exfoliative dermatitis.

Bullous dermatitis herpetiformis.

Severe seborrheic dermatitis.

Severe psoriasis.

Mycosis fungoides.

5. Allergic states. Control of severe or incapacitating allergic conditions intractable to adequate trials of conventional treatment in:

Bronchial asthma.

Contact dermatitis.

Atopic dermatitis.

Serum sickness.

Seasonal or perennial allergic rhinitis.

Drug hypersensitivity reactions.

Urticarial transfusion reactions.

Acute noninfectious laryngeal edema (epinephrine is the drug of first choice).

6. Ophthalmic diseases. Severe acute and chronic allergic and inflammatory processes involving the eye, such as:

Herpes zoster ophthalmicus.

Iritis, iridocyclitis.

Chorioretinitis.

Diffuse posterior uveitis and choroiditis.

Optic neuritis.

Sympathetic ophthalmia.

Anterior segment inflammation.

Allergic conjunctivitis.

Allergic corneal marginal ulcers.
Keratitis.

7. Gastrointestinal diseases. To tide the patient over a critical period of the disease in:

Ulcerative colitis (systemic therapy).

Regional enteritis (systemic therapy).

8. Respiratory diseases:

Symptomatic Sarcoidosis.

Berylliosis.

Fulminating or disseminated pulmonary tuberculosis when used concurrently with appropriate anti-tuberculosis chemotherapy.

Loeffler's syndrome not manageable by other means.

Aspiration pneumonitis.

9. Hematologic disorders:

Acquired (autoimmune) hemolytic anemia.

Idiopathic thrombocytopenic purpura in adults (I.V. only; I.M. administration is contraindicated).

Secondary thrombocytopenia in adults.

Erythroblastopenia (RBC anemia).

Congenital (erythroid) hypoplastic anemia.

10. Neoplastic diseases. For palliative management of:

Leukemias and lymphomas in adults.

Acute leukemia of childhood.

11. Edematous states. To induce diuresis or remission of proteinuria in the nephrotic syndrome, without uremia, of the idiopathic type or that due to lupus erythematosus.

12. Nervous system.

Acute exacerbations of multiple sclerosis.

13. Miscellaneous.

Tuberculous meningitis with subarachnoid block or impending block when used concurrently with appropriate anti-tuberculosis chemotherapy.

Trichinosis with neurologic or myocardial involvement.

Diagnostic testing of adrenocortical hyperfunction.

Cerebral edema of diverse etiologies in conjunction with adequate neurological evaluation and management.

B. Intra-articular or soft tissue administration. When the strength and dosage form of the drug lend the preparation to the treatment of the condition, those products labeled for intra-articular or soft tissue administration are indicated as adjunctive therapy for short-term administration (to tide the patient over an acute episode or exacerbation) in:

Synovitis of osteoarthritis.

Rheumatoid arthritis.

Acute and subacute bursitis.

Acute gouty arthritis.

Epicondylitis.

Acute nonspecific tenosynovitis.

Post-traumatic osteoarthritis.

C. Intralesional administration. When the strength and dosage form of the drug lend the preparation to the treatment of the condition, those products labeled for intralesional administration are indicated for:

Keloids.

Localized hypertrophic, infiltrated, inflammatory lesions of: lichen planus, psoriatic plaques, granuloma annulare, and lichen simplex chronicus (neurodermatitis).

Discoid lupus erythematosus.

Necrobiosis lipoidica diabeticorum.

Alopecia areata.

They also may be useful in cystic tumors of an aponeurosis tendon (ganglia).

CONTRAINDICATIONS

Systemic fungal infections.

WARNINGS

Serious Neurologic Adverse Reactions with Epidural Administration

Serious neurologic events, some resulting in death, have been reported with epidural injection of corticosteroids. Specific events reported include, but are not limited to, spinal cord infarction, paraplegia, quadriplegia, cortical blindness, and stroke. These serious neurologic events have been reported with and without use of fluoroscopy. The safety and effectiveness of epidural administration of corticosteroids have not been established, and corticosteroids are not approved for this use.

In patients on corticosteroid therapy subject to any unusual stress, increased dosage of rapidly acting corticosteroids before, during and after the stressful situation is indicated.

Prolonged use of corticosteroids may produce posterior subcapsular cataracts, glaucoma with possible damage to the optic nerves, and may enhance the establishment of secondary ocular infections due to fungi or viruses.

Immunosuppression and Increased Risk of Infection

Corticosteroids, including dexamethasone sodium phosphate, suppress the immune system and increase the risk of infection with any pathogen, including viral, bacterial, fungal, protozoan, or helminthic pathogens. Corticosteroids can:

- Reduce resistance to new infections
- Exacerbate existing infections
- Increase the risk of disseminated infections
- Increase the risk of reactivation or exacerbation of latent infections
- Mask some signs of infection

Corticosteroid-associated infections can be mild but can be severe and at times fatal. The rate of infectious complications increases with increasing corticosteroid dosages.

Monitor for the development of infection and consider dexamethasone sodium phosphate withdrawal or dosage reduction as needed.

Tuberculosis

If dexamethasone sodium phosphate is used to treat a condition in patients with latent tuberculosis or tuberculin reactivity, tuberculosis may occur. Closely monitor such patients for reactivation. During prolonged therapy, patients with latent tuberculosis or tuberculin reactivity should receive chemoprophylaxis.

Varicella Zoster and Measles Viral Infections

Varicella and measles can have a serious or even fatal course in non-immune patients taking corticosteroids, including dexamethasone sodium phosphate. In corticosteroid-treated patients who have not had these diseases or are non-immune, particular care should be taken to avoid exposure to varicella and measles:

- If a dexamethasone sodium phosphate-treated patient is exposed to varicella, prophylaxis with varicella zoster immune globulin may be indicated. If varicella develops, treatment with antiviral agents may be considered.
- If a dexamethasone sodium phosphate-treated patient is exposed to measles, prophylaxis with immunoglobulin may be indicated.

Hepatitis B Virus Reactivation

Hepatitis B virus reactivation can occur in patients who are hepatitis B carriers treated with immunosuppressive dosages of corticosteroids, including dexamethasone sodium phosphate. Reactivation can also occur infrequently in corticosteroid-treated patients who appear to have resolved hepatitis B infection.

Screen patients for hepatitis B infection before initiating immunosuppressive (e.g., prolonged) treatment with dexamethasone sodium phosphate. For patients who show evidence of hepatitis B infection, recommend consultation with physicians with expertise in managing hepatitis B regarding monitoring and consideration for hepatitis B antiviral therapy.

Fungal Infections

Corticosteroids, including dexamethasone sodium phosphate, may exacerbate systemic fungal infections; therefore, avoid dexamethasone sodium phosphate use in the presence of such infections unless dexamethasone sodium phosphate is needed to control drug reactions. For patients on chronic dexamethasone sodium phosphate therapy who develop systemic fungal infections, dexamethasone sodium phosphate withdrawal or dosage reduction is recommended.

Amebiasis

Corticosteroids, including dexamethasone sodium phosphate, may activate latent amebiasis. Therefore, it is recommended that latent amebiasis or active amebiasis be ruled out before initiating dexamethasone sodium phosphate in patients who have spent time in the tropics or patients with unexplained diarrhea.

Strongyloides Infestation

Corticosteroids, including dexamethasone sodium phosphate, should be used with great care in patients with known or suspected Strongyloides (threadworm) infestation. In such patients, corticosteroid-induced immunosuppression may lead to Strongyloides hyperinfection and dissemination with widespread larval migration, often accompanied by severe enterocolitis and potentially fatal gram-negative septicemia.

Cerebral Malaria

Avoid corticosteroids, including dexamethasone sodium phosphate, in patients with cerebral malaria.

Kaposi’s Sarcoma

Kaposi’s sarcoma has been reported to occur in patients receiving corticosteroid therapy, most often for chronic conditions. Discontinuation of corticosteroids may result in clinical improvement of Kaposi’s sarcoma.

Usage in Pregnancy. Since adequate human reproduction studies have not been done with corticosteroids, use of these drugs in pregnancy, nursing mothers or women of childbearing potential requires that the possible benefits of the drug be weighed against the potential hazards to the mother and embryo or fetus. Infants born of mothers who have received substantial doses of corticosteroids during pregnancy should be carefully observed for signs of hypoadrenalism.

Average and large doses of cortisone or hydrocortisone can cause elevation of blood pressure, salt and water retention, and increased excretion of potassium. These effects are less likely to occur with the synthetic derivatives except when used in large doses. Patients with a stressed myocardium should be observed carefully and the drug administered slowly since premature ventricular contractions may occur with rapid administration. Dietary salt restriction and potassium supplementation may be necessary. All corticosteroids increase calcium excretion.

While on corticosteroid therapy patients should not be vaccinated against smallpox. Other immunization procedures should not be undertaken in patients who are on corticosteroids, especially in high doses, because of possible hazards of neurological complications and lack of antibody response.

Because rare instances of anaphylactoid reactions have occurred in patients receiving parenteral corticosteroid therapy, appropriate precautionary measures should be taken prior to administration, especially when the patient has a history of allergy to any drug.

Dexamethasone sodium phosphate injection contains sodium sulfite, a sulfite that may cause allergic type reactions including anaphylactic symptoms and life-threatening or less severe asthmatic episodes in certain susceptible people. The overall prevalence of sulfite sensitivity in the general population is unknown and probably low. Sulfite sensitivity is seen more frequently in asthmatic than in nonasthmatic people.

PRECAUTIONS

Drug-induced secondary adrenocortical insufficiency may be minimized by gradual reduction of dosage. This type of relative insufficiency may persist for months after discontinuation of therapy; therefore, in any situation of stress occurring during that period, hormone therapy should be reinstituted. Since mineralocorticoid secretion may be impaired, salt and/or a mineralocorticoid should be administered concurrently.

There is an enhanced effect of corticosteroids in patients with hypothyroidism and in those with cirrhosis.

Corticosteroids should be used cautiously in patients with ocular herpes simplex for fear of corneal perforation.

The lowest possible dose of corticosteroid should be used to control the condition under treatment, and when reduction in dosage is possible, the reduction must be gradual.

Psychic derangements may appear when corticosteroids are used ranging from euphoria, insomnia, mood swings, personality changes, and severe depression to frank psychotic manifestations. Also, existing emotional instability or psychotic tendencies may be aggravated by corticosteroids.

Aspirin should be used cautiously in conjunction with corticosteroids in hypoprothrombinemia.

Steroids should be used with caution in nonspecific ulcerative colitis, if there is a probability of impending perforation, abscess or other pyogenic infection, also in diverticulitis, fresh intestinal anastomoses, active or latent peptic ulcer, renal insufficiency, hypertension, osteoporosis, and myasthenia gravis.

Growth and development of infants and children on prolonged corticosteroid therapy should be carefully followed.

Patients who are on immunosuppressant doses of corticosteroids should be warned to avoid exposure to chickenpox or measles and, if exposed, to obtain medical advice.

Intra-articular injection of a corticosteroid may produce systemic as well as local effects.

Appropriate examination of any joint fluid present is necessary to exclude a septic process.

A marked increase in pain accompanied by local swelling, further restriction of joint motion, fever, and malaise are suggestive of septic arthritis. If this complication occurs and the diagnosis of sepsis is confirmed, appropriate antimicrobial therapy should be instituted.

Local injection of a steroid into a previously infected joint is to be avoided. Corticosteroids should not be injected into unstable joints.

Although controlled clinical trials have shown corticosteroids to be effective in speeding the resolution of acute exacerbations of multiple sclerosis they do not show that they affect the ultimate outcome or natural history of the disease. The studies do show that relatively high doses of corticosteroids are necessary to demonstrate a significant effect. (See Dosage and Administration Section).

Since complications of treatment with glucocorticoids are dependent on the size of the dose and the duration of treatment a risk/benefit decision must be made in each individual case as to dose and duration of treatment and as to whether daily or intermittent therapy should be used.

ADVERSE REACTIONS

Fluid and electrolyte disturbances:

Sodium retention

Fluid retention

Congestive heart failure in susceptible patients

Potassium loss

Hypokalemic alkalosis

Hypertension

Musculoskeletal:

Muscle weakness

Steroid myopathy

Loss of muscle mass

Osteoporosis

Vertebral compression fractures

Aseptic necrosis of femoral and humeral heads

Pathologic fracture of long bones

Gastrointestinal:

Peptic ulcer with possible subsequent perforation and hemorrhage

Pancreatitis

Abdominal distention

Ulcerative esophagitis

Dermatological:

Impaired wound healing

Thin fragile skin

Facial erythema

Increased sweating

May suppress reactions to skin tests

Petechiae and ecchymoses

Neurological:
Convulsions
Increased intracranial pressure with papilledema (pseudotumor cerebri) usually after treatment

Vertigo

Headache

Ophthalmic:

Posterior subcapsular cataracts

Increased intraocular pressure

Glaucoma

Endocrine:

Menstrual irregularities

Development of cushingoid state

Suppression of growth in children
Secondary adrenocortical and pituitary unresponsiveness, particularly in times of stress, as in trauma, surgery, or illness

Decreased carbohydrate tolerance

Manifestations of latent diabetes mellitus

Increased requirements for insulin or oral hypoglycemic agents in diabetics

Metabolic:

Negative nitrogen balance due to protein catabolism

Miscellaneous:

Hyperpigmentation or hypopigmentation

Subcutaneous and cutaneous atrophy

Sterile abscess

Postinjection flare, following intra-articular use

Charcot-like arthropathy

Itching, burning, tingling in the ano-genital region

DOSAGE AND ADMINISTRATION

A. Intravenous or intramuscular administration. The initial dosage of dexamethasone sodium phosphate injection USP may vary from 0.50 mg/day to 9 mg/day depending on the specific disease entity being treated. In situations of less severity, lower doses will generally suffice while in selected patients higher initial doses may be required. Usually the parenteral dosage ranges are one-third to one-half the oral dose given every 12 hours. However, in certain overwhelming, acute, life-threatening situations, administration of dosages exceeding the usual dosages may be justified and may be in multiples of the oral dosages.

For the treatment of unresponsive shock high pharmacologic doses of this product are currently recommended. Reported regimens range from 1 to 6 mg/kg of body weight as a single intravenous injection to 40 mg initially followed by repeat intravenous injection every 2 to 6 hours while shock persists.

For the treatment of cerebral edema in adults an initial intravenous dose of 10 mg is recommended followed by 4 mg intramuscularly every six hours until maximum response has been noted. This regimen may be continued for several days postoperatively in patients requiring brain surgery. Oral dexamethasone, 1 to 3 mg t.i.d., should be given as soon as possible and dosage tapered off over a period of five to seven days. Nonoperative cases may require continuous therapy to remain free of symptoms of increased intracranial pressure. The smallest effective dose should be used in children, preferably orally. This may approximate 0.2 mg/kg/24 hours in divided doses.

In treatment of acute exacerbations of multiple sclerosis daily doses of 200 mg of prednisolone for a week followed by 80 mg every other day or 4 to 8 mg dexamethasone every other day for 1 month have been shown to be effective.

The initial dosage should be maintained or adjusted until a satisfactory response is noted. If after a reasonable period of time there is a lack of satisfactory clinical response, dexamethasone sodium phosphate injection USP should be discontinued and the patient transferred to other appropriate therapy. It should be emphasized that dosage requirements are variable and must be individualized on the basis of the disease under treatment and the response of the patient.

After a favorable response is noted, the proper maintenance dosage should be determined by decreasing the initial drug dosage in small decrements at appropriate time intervals until the lowest dosage which will maintain an adequate clinical response is reached. It should be kept in mind that constant monitoring is needed in regard to drug dosage. Included in the situations which may make dosage adjustments necessary are changes in clinical status secondary to remissions or exacerbations in the disease process, the patient’s individual drug responsiveness and the effect of patient exposure to stressful situations not directly related to the disease entity under treatment. In this later situation it may be necessary to increase the dosage of dexamethasone sodium phosphate injection USP for a period of time consistent with the patient’s condition. If after a long-term therapy the drug is to be stopped, it is recommended that it be withdrawn gradually rather than abruptly.

B. Intra-articular, soft tissue or intralesional administration. The dose for instrasynovial administration is usually 2 to 4 mg for large joints and 0.8 to 1 mg for small joints. For soft tissue and bursal injections a dose of 2 to 4 mg is recommended. Ganglia require a dose of 1 to 2 mg. A dose of 0.4 to 1 mg is used for injection into tendon sheaths. Injection into intervertebral joints should not be attempted at any time and hip joint injection cannot be recommended as an office procedure.

Intrasynovial and soft tissue injections should be employed only when affected areas are limited to 1 or 2 sites. It should be remembered that corticoids provide palliation only and that other conventional or curative methods of therapy should be employed when indicated.

Parenteral drug products should be inspected visually for particulate matter and discoloration prior to administration, whenever solution and container permit.

Frequency of injection usually ranges from once every 3 to 5 days to once every 2 to 3 weeks. Frequent intra-articular injection may cause damage to joint tissue.

HOW SUPPLIED

Product: 50090-3300

NDC: 50090-3300-0 30 mL in a VIAL, MULTI-DOSE / 25 in a CARTON